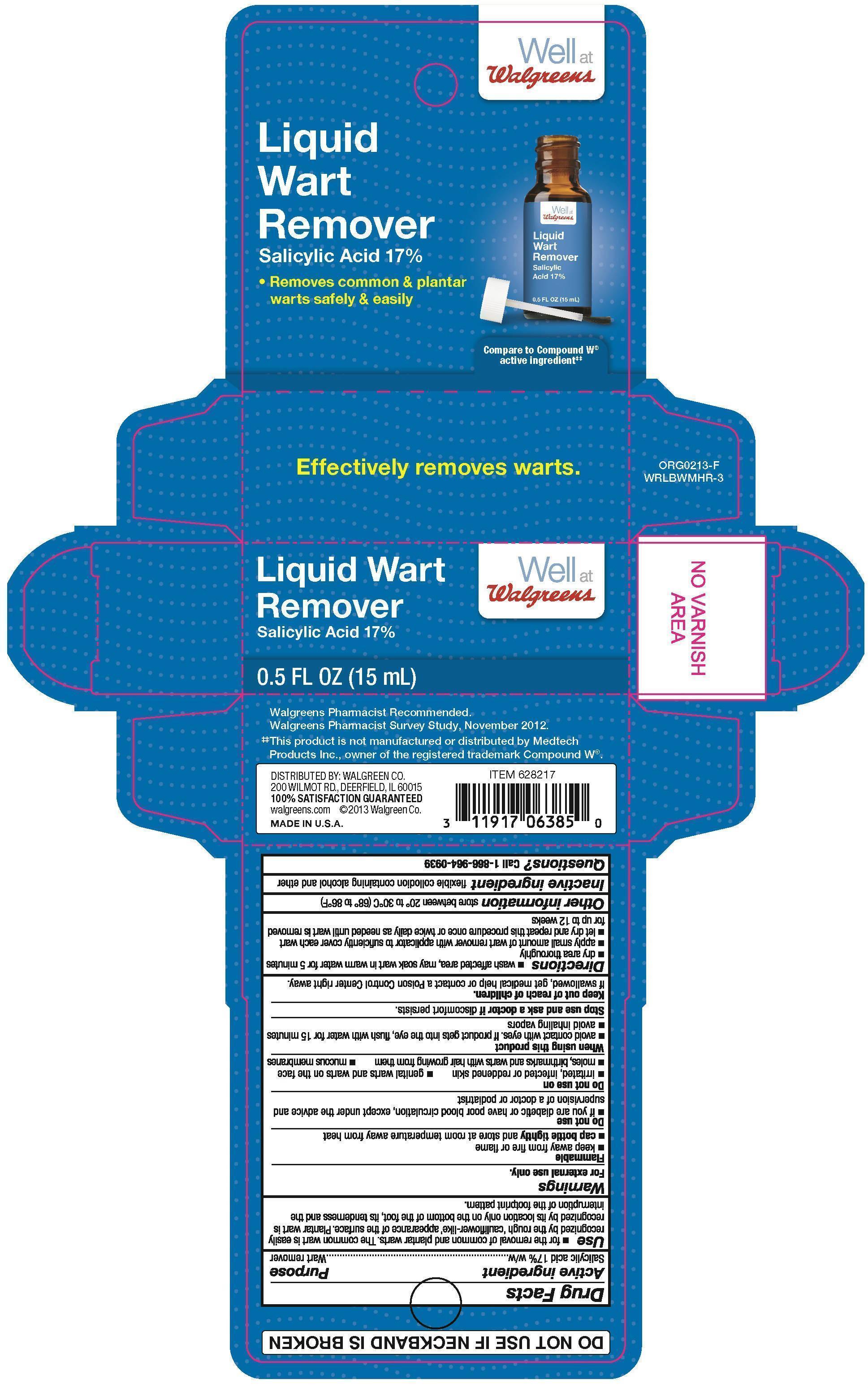 DRUG LABEL: Salicylic Acid
NDC: 0363-8217 | Form: LIQUID
Manufacturer: Walgreen Company
Category: otc | Type: HUMAN OTC DRUG LABEL
Date: 20251007

ACTIVE INGREDIENTS: SALICYLIC ACID 0.17 g/1 g
INACTIVE INGREDIENTS: PYROXYLIN; CAMPHOR (NATURAL); CASTOR OIL

Walgreens Liquid Wart Remover

Active ingredient

Salicylic acid 17%w/w

Purpose

Wart remover

Uses

- for the removal of common and plantar warts. The common wart is easily recognized by the rough 'cauliflower-like' appearance of the surface. Plantar wart is recognized by its location only on the bottom of the foot, its tenderness and the interruption of the footprint pattern.

Warnings

For external use only.

Flammable

- keep away from fire or flame
- cap bottle tightly and store at room temperature away from heat

Do not use

- if you are a diabetic or have poor blood circulation, except under the advice and supervision of a doctor or podiatrist
- on irritated, infected or reddened skin
- on genital warts and warts on the face
- on moles, birthmarks and warts with hair growing from them
- on mucous membranes

When using this product

- avoid contact with eyes. If product get into eyes, flush with water for 15 minutes
- avoid inhaling vapors

Keep out of reach of children.

If swallowed, get medical help or contact a Poison Control Center right away.

Directions

- wash affected area, may soak wart in warm water for 5 minutes
- dry area thoroughly
- apply small amount of wart remover with applicator to sufficiently cover each wart
- let dry and repeat this procedure once or twice daily until wart is removed for up to 12 weeks

Other information

store between 20°C to 30°C (68°F to 86°F)

Inactive ingredients

camphor, castro oil, ethanol, ethyl ether, nitrocellulose

Questions?

Call 1-866-964-0939

Principal Display Panel

Well at Walgreens
Liquid wart remover
Salicylic Acid 17%

- Removes Common & plantar warts safely & easily

Effectively removes warts.

0.5 FL OZ (15mL)